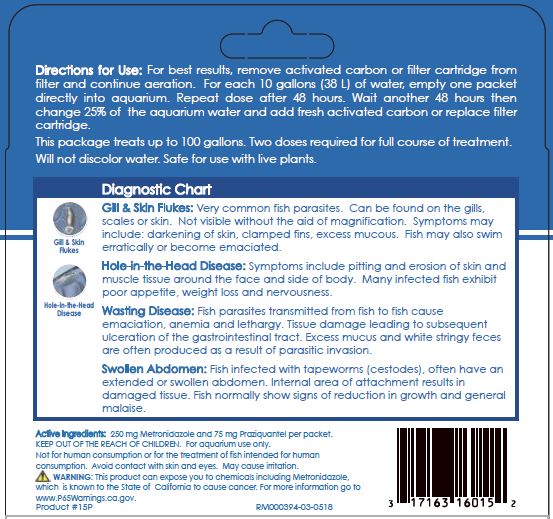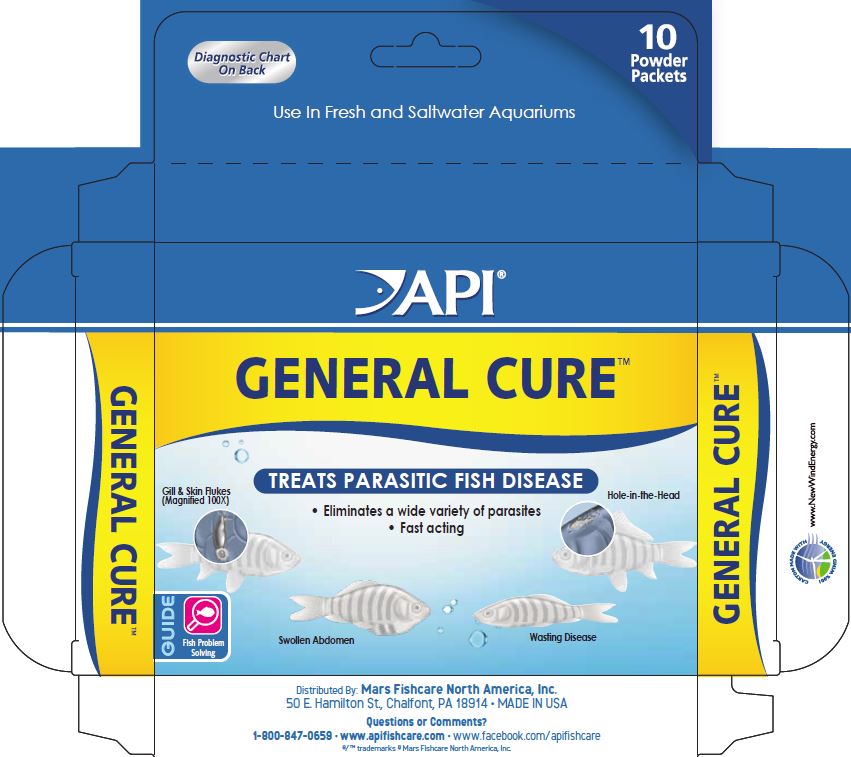 DRUG LABEL: API General Cure
NDC: 17163-015 | Form: POWDER
Manufacturer: MARS FISHCARE NORTH AMERICA, INC.
Category: animal | Type: OTC ANIMAL DRUG LABEL
Date: 20220419

ACTIVE INGREDIENTS: METRONIDAZOLE 250 mg/2 g; PRAZIQUANTEL 75 mg/2 g

Drug Label

ACTIVE INGREDIENT

Active Ingredients: 250 mg Metronidazole and 75 mg Praziquantel per packet.

DOSAGE AND ADMINISTRATION

Directions for Use:

For best results, remove activated carbon or filter cartridge from filter and continue aeration.

For each 10 gallons (38 L) of water, empty one packet directly into aquarium.

Repeat dose after 48 hours.

Wait another 48 hours then change 25% of the aquarium water and add fresh activated carbon or replace filter cartridge.

This package treats up to 100 gallons.

Two doses required for full course of treatment.

Will not discolor water

Safe for use with live plants.

INDICATIONS AND USAGE

Diagnostic Chart

Gill and Skin Flukes:

Very common fish parasite. Can be found on the gills, scales or skin. Not visible without the aid of magnification. Symptoms may include: darkening of skin, clamped fins, excess mucous. Fish may also swim erratically or become emaciated.

Hole-in-the-Head Disease:

Symptoms include pitting and erosion of skin and muscle tissue around the face and side of body. Many infected fish exhibit poor appetite, weight loss and nervousness.

Wasting Disease:

Fish parasites transmitted from fish to fish cause emaciation, anemia and lethargy. Tissue damage leading to subsequent ulceration of the gastrointestinal tract. Excess mucus and white stringy feces are often produced as a result of parasitic invasion.

Swollen Abdomen:

Fish infected with tapeworms (cestodes), often have an extended or swollen abdomen. Internal areas of attachment results in damaged tissue. Fish normally show signs of reduction in growth and general malaise.

WARNINGS AND PRECAUTIONS

KEEP OUT OF THE REACH OF CHILDREN.

For aquarium use only.

Not for human consumption or for the treatment of fish intended for human consumption.

Avoid contact with skin and eyes.

May cause irritation.

! WARNING:

This product can expose you to chemicals including Metronidazole, which is known to the State of California to cause cancer.

For more information go to www.P65Warnings.ca.gov.

PACKAGE LABEL

Diagnostic Chart

On Back

10

Powder

Packets

Use In Fresh and Saltwater Aquariums

API

GENERAL CURE

TREATS PARASITIC FISH DISEASE

Eliminates a wide variety of parasites

Fast acting

Gill and Skin Flukes

Hole-in-the-Head

Swollen Abdomen

Wasting Disease

GUIDE

Fish Problem

Solving